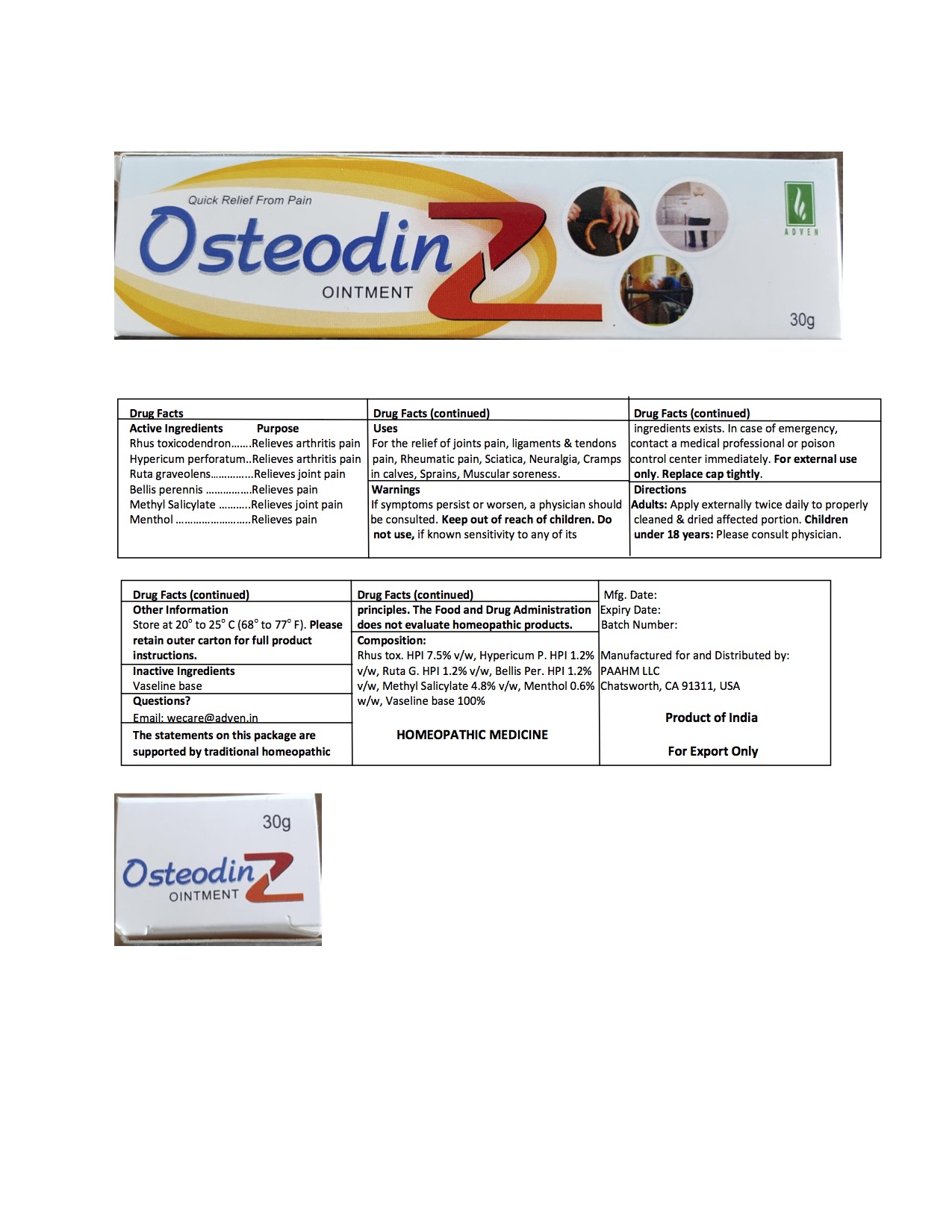 DRUG LABEL: osteodin-z
NDC: 69825-003 | Form: OINTMENT
Manufacturer: Adven Biotech Private Limited
Category: homeopathic | Type: HUMAN OTC DRUG LABEL
Date: 20160208

ACTIVE INGREDIENTS: HYPERICUM PERFORATUM 0.36 g/30 g; RUTA GRAVEOLENS WHOLE 0.36 g/30 g; BELLIS PERENNIS 0.36 g/30 g; TOXICODENDRON PUBESCENS LEAF 2.25 g/30 g; MENTHOL 0.18 g/30 g
INACTIVE INGREDIENTS: METHYL SALICYLATE 1.44 g/30 g

DOSAGE AND ADMINISTRATION

Adults: Apply externally twice daily to properly cleaned & dried affected portion.

Children under 18 years: Please consult physician.

WARNINGS

If symptons persist or worsen, a physician should be consulted. Keep out of reach of children. Do not use, if known sentivity to any of its ingredients exists. In case of emergency, contact a medical professional or posion control center immediately. For external use only. Replace cap tightly.

INACTIVE INGREDIENT

Vaseline base

PURPOSE

Relieves arthritis pain

Relieves joint pain

Relieves pain

ACTIVE INGREDIENT

Rhus toxicondendron, Hypericum perforatum, Ruta graveolens, Bellis pernnis, Menthol

INDICATIONS AND USAGE

For the relief of joins pain, ligaments & tendons pain, Rheumatic pain, Sciatica, Neuralgia, Cramps in calves, Sprains, Muscular soreness.